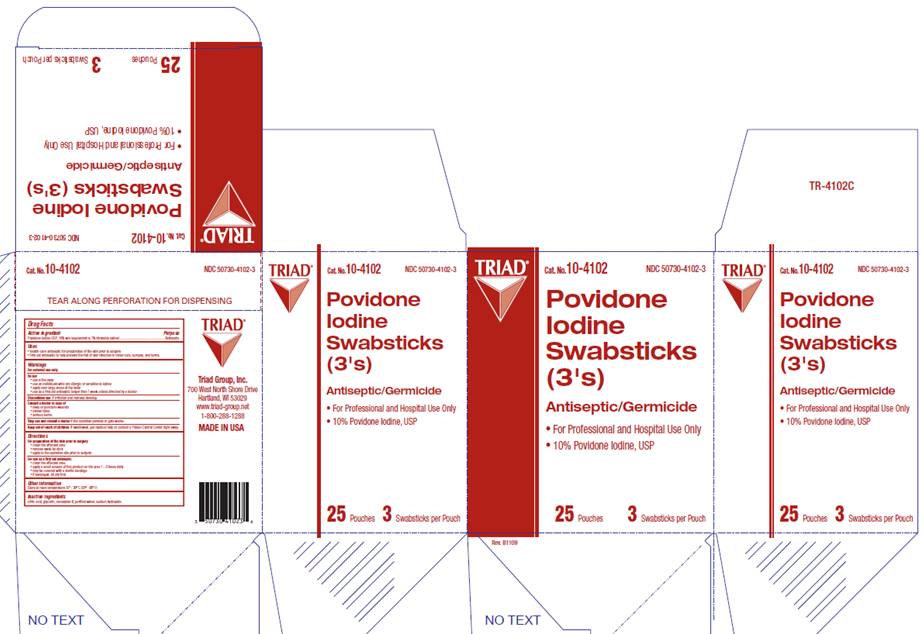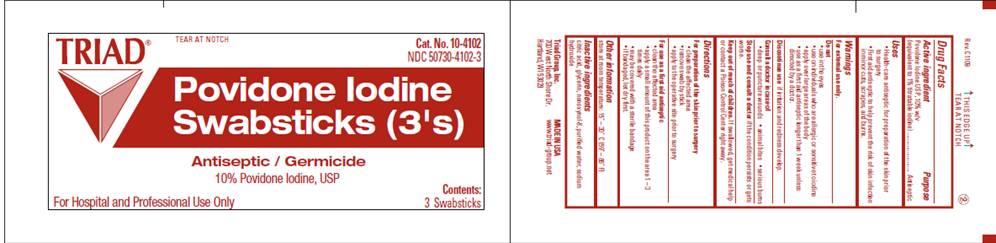 DRUG LABEL: Povidone-Iodine Prep Swabsticks
NDC: 50730-4102 | Form: SOLUTION
Manufacturer: Triad Group
Category: otc | Type: HUMAN OTC DRUG LABEL
Date: 20100322

ACTIVE INGREDIENTS: povidone-iodine 0.10 mg/1 mL
INACTIVE INGREDIENTS: citric acid monohydrate; glycerin; sodium hydroxide; water

DRUG FACTS

ACTIVE INGREDIENT

Povidone Iodine USP 10% w/v (equivalent to 1% titratable iodine)

PURPOSE

Antiseptic

USES

- Health Care Antiseptic for preparation of the skin prior to surgery

- First Aid Antiseptic to help prevent the risk of infection in minor cuts, scrapes and burns

WARNINGS

For external use only.

Do not

- use in the eyes
- apply over large areas of the body
- use on individuals who are allergic or sensitive to iodine
- use as a first aid antiseptic for longer than 1 week unless directed by a doctor

Ask a doctor in case of

- deep or puncture wounds
- animal bites
- serious burns

Stop use and ask a doctor

- if condition persists for more than 72 hours
- if irritation and redness develop

Keep out of reach of children

If swallowed, get medical help or contact a Poison Control Center right away.

DIRECTIONS

For preparation of the skin prior to surgery

- clean the affected area
- remove swab by stick
- apply to the operative site prior to surgery

As a first aid antiseptic

- clean the affected area
- apply a small amount of this product to the area 1-3 times daily
- may be covered with a sterile bandage
- if bandaged, let dry first

OTHER INFORMATION

Store at room temperature 15° - 30° C (59° - 86° F)

INACTIVE INGREDIENTS

citric acid, glycerin, nonoxynol-8, purified water, sodium hydroxide

POUCH INFORMATION

TRIAD
Cat. No. 10-4102
NDC 50730-4102-3
10% Povidone Iodine, USP
POVIDONE IODINE
SWABSTICKS (3's)
Antiseptic / Germicide
10% Povidone Iodine, USP
For Hospital and Professional Use Only
Contents:
3 Swabsticks
Triad Group, Inc.
700 West North Shore Drive
Hartland, WI 53029
MADE IN USA
www.triad-group.net

CARTON INFORMATION

TRIAD
Cat. No. 10-4102
NDC 50730-4102-3
POVIDONE IODINE
SWABSTICKS (3's)
Antiseptic / Germicide
For Hospital and Professional Use
10% Povidone Iodine, USP
25 Pouches
3 Swabsticks per Pouch